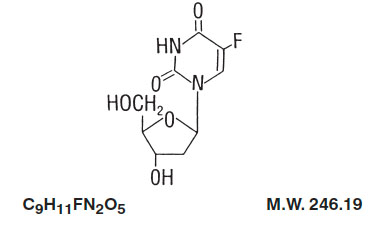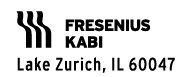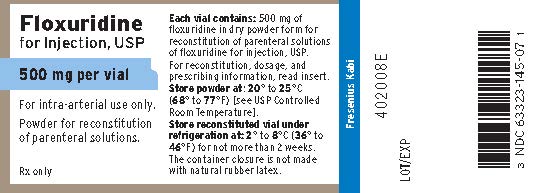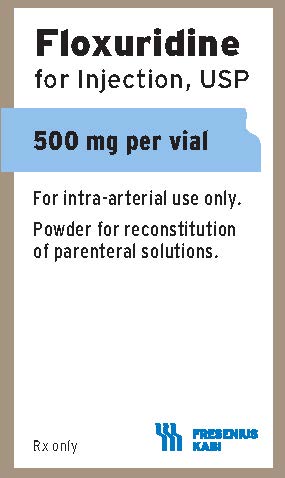 DRUG LABEL: Floxuridine

NDC: 63323-145 | Form: INJECTION, POWDER, LYOPHILIZED, FOR SOLUTION
Manufacturer: Fresenius Kabi USA, LLC
Category: prescription | Type: HUMAN PRESCRIPTION DRUG LABEL
Date: 20241014

ACTIVE INGREDIENTS: FLOXURIDINE 500 mg/5 mL

Floxuridine for Injection, USP

FOR INTRA-ARTERIAL INFUSION ONLY

WARNING
It is recommended that Floxuridine for Injection, USP be given only by or under the supervision of a qualified physician who is experienced in cancer chemotherapy and intra-arterial drug therapy and is well versed in the use of potent antimetabolites.
Because of the possibility of severe toxic reactions, all patients should be hospitalized for initiation of the first course of therapy.

DESCRIPTION:

Floxuridine for Injection, USP, an antineoplastic antimetabolite, is available as a sterile, nonpyrogenic, lyophilized powder for reconstitution. Each vial contains 500 mg of floxuridine which is to be reconstituted with 5 mL of sterile water for injection. An appropriate amount of reconstituted solution is then diluted with a parenteral solution for intra-arterial infusion (see DOSAGE AND ADMINISTRATION).

Floxuridine is a fluorinated pyrimidine. Chemically, floxuridine is 2’-deoxy-5-fluorouridine. It is a white to off-white odorless solid which is freely soluble in water. The 2% aqueous solution has a pH of between 4.0 and 5.5.

The structural formula is:

CLINICAL PHARMACOLOGY:

When floxuridine is given by rapid intra-arterial injection it is apparently rapidly catabolized to 5-fluorouracil. Thus, rapid injection of floxuridine produces the same toxic and antimetabolic effects as does 5-fluorouracil. The primary effect is to interfere with the synthesis of deoxyribonucleic acid (DNA) and to a lesser extent inhibit the formation of ribonucleic acid (RNA). However, when floxuridine is given by continuous intra-arterial infusion its direct anabolism to floxuridine-monophosphate is enhanced, thus increasing the inhibition of DNA.

Floxuridine is metabolized in the liver. The drug is excreted intact and as urea, fluorouracil, α-fluoro-β-ureidopropionic acid, dihydrofluorouracil, α-fluoro-β-guanidopropionic acid and α-fluoro-β-alanine in the urine; it is also expired as respiratory carbon dioxide. Pharmacokinetic data on intra-arterial infusion of floxuridine are not available.

INDICATIONS AND USAGE:

Floxuridine for Injection, USP is effective in the palliative management of gastrointestinal adenocarcinoma metastatic to the liver, when given by continuous regional intra-arterial infusion in carefully selected patients who are considered incurable by surgery or other means. Patients with known disease extending beyond an area capable of infusion via a single artery should, except in unusual circumstances, be considered for systemic therapy with other chemotherapeutic agents.

CONTRAINDICATIONS:

Floxuridine therapy is contraindicated for patients in a poor nutritional state, those with depressed bone marrow function or those with potentially serious infections.

WARNINGS:

BECAUSE OF THE POSSIBILITY OF SEVERE TOXIC REACTIONS, ALL PATIENTS SHOULD BE HOSPITALIZED FOR THE FIRST COURSE OF THERAPY.

Floxuridine should be used with extreme caution in poor risk patients with impaired hepatic or renal function or a history of high-dose pelvic irradiation or previous use of alkylating agents. The drug is not intended as an adjuvant to surgery.

Floxuridine may cause fetal harm when administered to a pregnant woman. It has been shown to be teratogenic in the chick embryo, mouse (at doses of 2.5 to 100 mg/kg) and rat (at doses of 75 to 150 mg/kg). Malformations included cleft palates; skeletal defects; and deformed appendages, paws and tails. The dosages which were teratogenic in animals are 4.2 to 125 times the recommended human therapeutic dose.

There are no adequate and well-controlled studies with floxuridine in pregnant women. If this drug is used during pregnancy or if the patient becomes pregnant while taking (receiving) this drug, the patient should be apprised of the potential hazard to the fetus. Women of childbearing potential should be advised to avoid becoming pregnant.

Combination Therapy

Any form of therapy which adds to the stress of the patient, interferes with nutrition or depresses bone marrow function will increase the toxicity of floxuridine.

PRECAUTIONS:

General

Floxuridine is a highly toxic drug with a narrow margin of safety. Therefore, patients should be carefully supervised since therapeutic response is unlikely to occur without some evidence of toxicity. Severe hematological toxicity, gastrointestinal hemorrhage and even death may result from the use of floxuridine despite meticulous selection of patients and careful adjustment of dosage. Although severe toxicity is more likely in poor risk patients, fatalities may be encountered occasionally even in patients in relatively good condition.

Therapy is to be discontinued promptly whenever one of the following signs of toxicity appears:

Myocardial ischemia

Stomatitis or esophagopharyngitis, at the first visible sign

Leukopenia (WBC under 3,500) or a rapidly falling white blood count

Vomiting, intractable

Diarrhea, frequent bowel movements or watery stools

Gastrointestinal ulceration and bleeding

Thrombocytopenia (platelets under 100,000)

Hemorrhage from any site

Information for Patients

Patients should be informed of expected toxic effects, particularly oral manifestations. Patients should be alerted to the possibility of alopecia as a result of therapy and should be informed that it is usually a transient effect.

Laboratory Tests

Careful monitoring of the white blood count and platelet count is recommended.

Drug Interactions

See WARNINGS.

Carcinogenesis, Mutagenesis, Impairment of Fertility

Carcinogenesis

Long-term studies in animals to evaluate the carcinogenic potential of floxuridine have not been conducted. On the basis of the available data, no evaluation can be made of the carcinogenic risk of floxuridine to humans.

Mutagenesis

Oncogenic transformation of fibroblasts from mouse embryo has been induced in vitro by floxuridine, but the relationship between oncogenicity and mutagenicity is not clear. Floxuridine has also been shown to be mutagenic in human leukocytes in vitro and in the Drosophila test system. In addition, 5-fluorouracil, to which floxuridine is catabolized when given by intraarterial injection, has been shown to be mutagenic in in vitro tests.

Impairment of Fertility

The effects of floxuridine on fertility and general reproductive performance have not been studied in animals. However, because floxuridine is catabolized to 5-fluorouracil, it should be noted that 5-fluorouracil has been shown to induce chromosomal aberrations and changes in chromosome organization of spermatogonia in rats at doses of 125 or 250 mg/kg, administered intraperitoneally.

Spermatogonial differentiation was also inhibited by fluorouracil, resulting in transient infertility. In female rats, fluorouracil, administered intraperitoneally at doses of 25 or 50 mg/kg during the preovulatory phase of oogenesis, significantly reduced the incidence of fertile matings, delayed the development of pre- and post-implantation embryos, increased the incidence of preimplantation lethality and induced chromosomal anomalies in these embryos. Compounds such as floxuridine, which interfere with DNA, RNA and protein synthesis, might be expected to have adverse effects on gametogenesis.

Pregnancy

Teratogenic Effects: Pregnancy category D.

See WARNINGS. Floxuridine has been shown to be teratogenic in the chick embryo, mouse (at doses of 2.5 to 100 mg/kg) and rat (at doses of 75 to 150 mg/kg). Malformations included cleft palates, skeletal defects and deformed appendages, paws and tails. The dosages which were teratogenic in animals are 3.2 to 125 times the recommended human therapeutic dose.

There are no adequate and well-controlled studies with floxuridine in pregnant women. While there is no evidence of teratogenicity in humans due to floxuridine, it should be kept in mind that other drugs which inhibit DNA synthesis (eg, methotrexate and aminopterin) have been reported to be teratogenic in humans. Floxuridine should be used during pregnancy only if the potential benefit justifies the potential risk to the fetus.

Nonteratogenic Effects

Floxuridine has not been studied in animals for its effects on peri- and postnatal development. However, compounds which inhibit DNA, RNA and protein synthesis might be expected to have adverse effects on peri- and postnatal development.

Nursing Mothers

It is not known whether floxuridine is excreted in human milk. Because floxuridine inhibits DNA and RNA synthesis, mothers should not nurse while receiving this drug.

Pediatric Use

Safety and effectiveness in pediatric patients have not been established.

ADVERSE REACTIONS:

Adverse reactions to the arterial infusion of floxuridine are generally related to the procedural complications of regional arterial infusion.

The more common adverse reactions to the drug are nausea, vomiting, diarrhea, enteritis, stomatitis and localized erythema. The more common laboratory abnormalities are anemia, leukopenia, thrombocytopenia and elevations of alkaline phosphatase, serum transaminase, serum bilirubin and lactic dehydrogenase.

Other adverse reactions are:

Gastrointestinal: duodenal ulcer, duodenitis, gastritis, bleeding, gastroenteritis, glossitis, pharyngitis, anorexia, cramps, abdominal pain; possible intra- and extrahepatic biliary sclerosis, as well as acalculous cholecystitis.

Dermatologic: alopecia, dermatitis, nonspecific skin toxicity, rash.

Cardiovascular: myocardial ischemia.

Miscellaneous Clinical Reactions: fever, lethargy, malaise, weakness.

Laboratory Abnormalities: BSP, prothrombin, total proteins, sedimentation rate and thrombopenia.

Procedural Complications of Regional Arterial Infusion: arterial aneurysm; arterial ischemia; arterial thrombosis; embolism; fibromyositis; thrombophlebitis; hepatic necrosis; abscesses; infection at catheter site; bleeding at catheter site; catheter blocked, displaced or leaking.

The following adverse reactions have not been reported with floxuridine but have been noted following the administration of 5-fluorouracil. While the possibility of these occurring following floxuridine therapy is remote because of its regional administration, one should be alert for these reactions following the administration of floxuridine because of the pharmacological similarity of these two drugs: pancytopenia, agranulocytosis, myocardial ischemia, angina, anaphylaxis, generalized allergic reactions, acute cerebellar syndrome, nystagmus, headache, dry skin, fissuring, photosensitivity, pruritic maculopapular rash, increased pigmentation of the skin, vein pigmentation, lacrimal duct stenosis, visual changes, lacrimation, photophobia, disorientation, confusion, euphoria, epistaxis and nail changes, including loss of nails.

OVERDOSAGE:

The possibility of overdosage with floxuridine is unlikely in view of the mode of administration. Nevertheless, the anticipated manifestations would be nausea, vomiting, diarrhea, gastrointestinal ulceration and bleeding, bone marrow depression (including thrombocytopenia, leukopenia and agranulocytosis). No specific antidotal therapy exists. Patients who have been exposed to an overdosage of floxuridine should be monitored hematologically for at least 4 weeks. Should abnormalities appear, appropriate therapy should be utilized.
The acute intravenous toxicity of floxuridine is as follows:

Species | LD50 (mg/kg ± S.E.)
Mouse | 880 ± 51
Rat | 670 ± 73
Rabbit | 94 ± 19.6
Dog | 157 ± 46

DOSAGE AND ADMINISTRATION:

Each vial must be reconstituted with 5 mL of sterile water for injection to yield a solution containing approximately 100 mg of floxuridine/mL. The calculated daily dose(s) of the drug is then diluted with 5% dextrose or 0.9% sodium chloride injection to a volume appropriate for the infusion apparatus to be used. The administration of floxuridine is best achieved with the use of an appropriate pump to overcome pressure in large arteries and to ensure a uniform rate of infusion.

Parenteral drug products should be inspected visually for particulate matter and discoloration prior to administration whenever solution and container permit.

The recommended therapeutic dosage schedule of floxuridine by continuous arterial infusion is 0.1 to 0.6 mg/kg/day. The higher dosage ranges (0.4 to 0.6 mg) are usually employed for hepatic artery infusion because the liver metabolizes the drug, thus reducing the potential for systemic toxicity. Therapy can be given until adverse reactions appear. (See PRECAUTIONS). When these side effects have subsided, therapy may be resumed. The patients should be maintained on therapy as long as response to floxuridine continues.

Procedures for proper handling and disposal of anticancer drugs should be considered. Several guidelines on this subject have been published.^1-7 There is no general agreement that all of the procedures recommended in the guidelines are necessary or appropriate.

HOW SUPPLIED:

Product No. | NDC No.
104507 | 63323-145-07 | Floxuridine for Injection, USP, 500 mg floxuridine powder in a 5 mL vial, packaged individually. This is to be reconstituted with 5 mL sterile water for injection.

The container closure is not made with natural rubber latex.

The sterile powder should be stored at 20° to 25°C (68° to 77°F) [see USP Controlled Room Temperature]. Reconstituted vials should be stored under refrigeration 2° to 8°C (36° to 46°F) for not more than 2 weeks.

REFERENCES:

1. Recommendations for the safe handling of parenteral antineoplastic drugs. Washington, DC, US Government Printing Office NIH publication 83-2621.
2. AMA Council Report. Guidelines for handling parenteral antineoplastics. JAMA. Mar 15, 1985, 253:1590-1592.
3. National Study Commission on Cytotoxic Exposure: Recommendations for handling cytotoxic agents. Available from Louis P. Jeffrey, ScD, Director of Pharmacy Services, Rhode Island Hospital, 593 Eddy Street, Providence, Rhode Island 02902.
4. Clinical Oncological Society of Australia: Guidelines and recommendations for safe handling of antineoplastic agents. Med J Aust. Apr 30, 1983, 1:426-428.
5. Jones, RB, Frank R, Mass T: Safe handling of chemotherapeutic agents: a report from the Mount Sinai Medical Center. CA. Sept-Oct, 1983, 33:258-263.
6. ASHP technical assistance bulletin on handling cytotoxic drugs in hospitals. AM J Hosp Pharm. Jan, 1985, 42:131-137.
7. OSHA Work-Practice Guidelines for Personnel Dealing with Cytotoxic (Antineoplastic) Drugs. Am J Hosp Pharm. 1986; 43:1193-1204.

www.fresenius-kabi.us
45914D

Revised: August 2016

PACKAGE LABEL

PACKAGE LABEL - PRINCIPAL DISPLAY - Floxuridine 500 mg Vial Label
Floxuridine for Injection, USP
500 mg per vial
For intra-arterial use only.
Powder for reconstitution of parenteral solutions.
Rx only

PACKAGE LABEL - PRINCIPAL DISPLAY - Floxuridine 500 mg Vial Carton Panel
Floxuridine for Injection, USP
500 mg per vial
For intra-arterial use only.
Powder for reconstitution of parenteral solutions.
Rx only